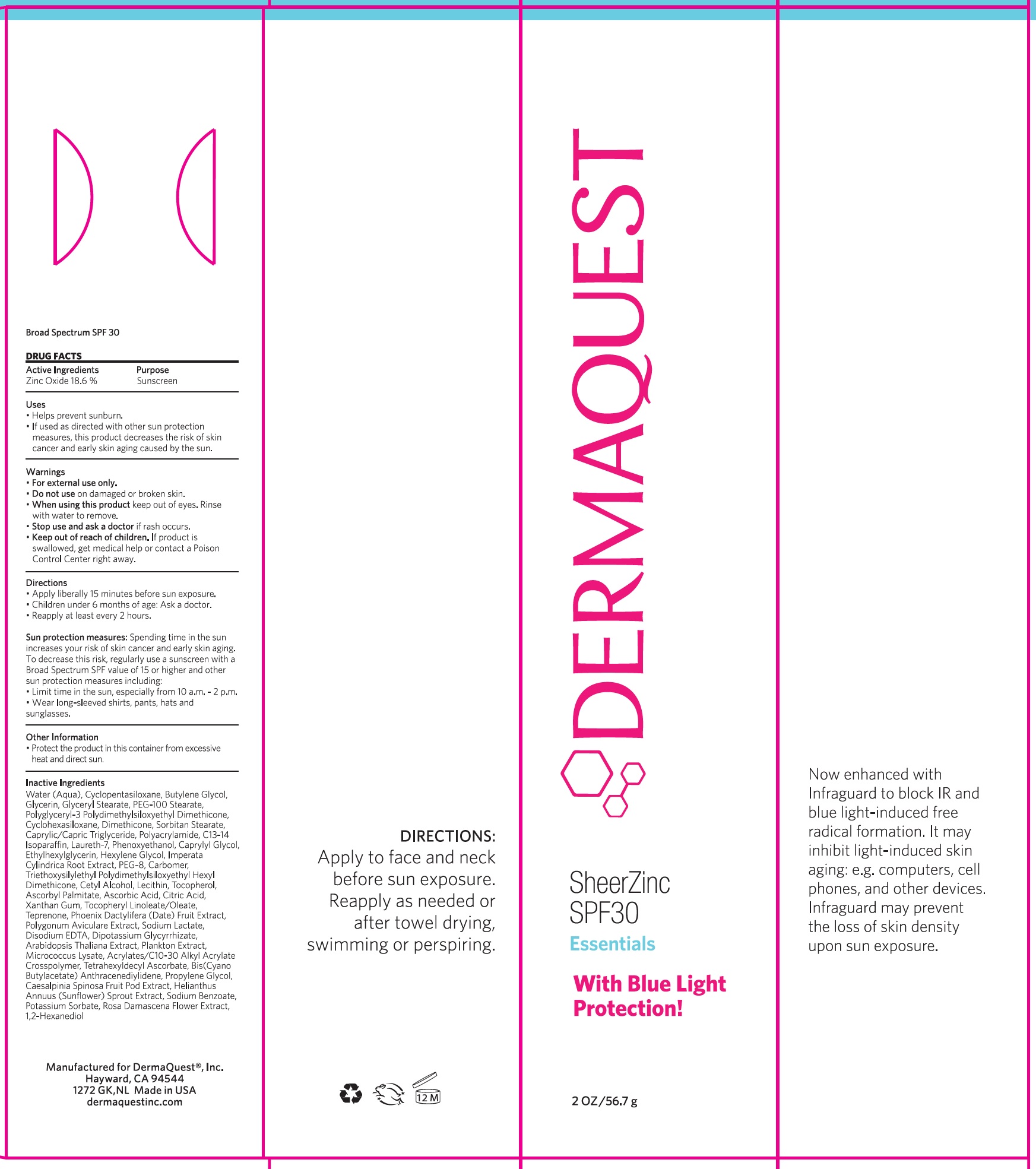 DRUG LABEL: Sheer Zinc SPF 30
NDC: 62742-4199 | Form: CREAM
Manufacturer: Allure Labs
Category: otc | Type: HUMAN OTC DRUG LABEL
Date: 20241209

ACTIVE INGREDIENTS: ZINC OXIDE 186 mg/1 g
INACTIVE INGREDIENTS: BUTYLENE GLYCOL; CYCLOMETHICONE 5; GLYCERYL MONOSTEARATE; SORBITAN MONOSTEARATE; CAPRYLYL GLYCOL; IMPERATA CYLINDRICA ROOT; C13-14 ISOPARAFFIN; ETHYLHEXYLGLYCERIN; HEXYLENE GLYCOL; CARBOMER INTERPOLYMER TYPE A (ALLYL SUCROSE CROSSLINKED); BUTYL CYANOACETATE; HELIANTHUS ANNUUS SPROUT; SODIUM BENZOATE; ASCORBIC ACID; 1,2-HEXANEDIOL; PHENOXYETHANOL; WATER; POLYGLYCERYL-3 POLYDIMETHYLSILOXYETHYL DIMETHICONE (4000 MPA.S); MEDIUM-CHAIN TRIGLYCERIDES; GLYCERIN; PEG-100 STEARATE; POLYACRYLAMIDE (10000 MW); LAURETH-7; GLYCYRRHIZINATE DIPOTASSIUM; MICROCOCCUS LUTEUS; TOCOPHEROL; DIMETHICONE; POLYETHYLENE GLYCOL 400; CETYL ALCOHOL; CITRIC ACID MONOHYDRATE; XANTHAN GUM; .ALPHA.-TOCOPHEROL LINOLEATE, D-; POLYGONUM AVICULARE TOP; CYCLOMETHICONE 6; ROSA DAMASCENA FLOWER; SODIUM LACTATE; DATE; ASCORBYL PALMITATE; TEPRENONE; EDETATE DISODIUM ANHYDROUS; ARABIDOPSIS THALIANA; POTASSIUM SORBATE; CAESALPINIA SPINOSA FRUIT POD; TETRAHEXYLDECYL ASCORBATE; CARBOXYPOLYMETHYLENE; LECITHIN, SOYBEAN

Drug Facts

Active Ingredients

Zinc Oxide 18.6%

Purpose:

Sunscreen

Uses:

- Helps prevent Sunburn.
- If used as directed with other sun protection measures, this product decreases the risk of skin cancer and early aging caused by sun.

WARNINGS

Warnigs:

- For external use only.

Do not use on damaged or broken skin.

When using this product keep out of eyes. Rinse with water to remove.

Stop use and ask a doctor if rash occurs.

Keep out of reach of children. If product is swallowed, get medical help or contact a Poison Control Center right away.

Directions:

- Apply liberally 15 minutes before sun exposure.
- Children under 6 months of age: Ask a Doctor
- Reapply at least every 2 hours.

Other Information

- Protect the product in this container from excessive heat and direct sun.

INACTIVE INGREDIENT

Inactive Ingredients: Water (Aqua), Cyclopentasiloxane , Butylene Glycol, Glycerin , Glyceryl Stearate, PEG-100 Stearate, Polyglyceryl-3 Polydimethylsiloxyethyl Dimethicone , Cyclohexasiloxane , Dimethicone , Sorbitan Stearate , Caprylic/Capric Triglyceride, Polyacrylamide, C13-14 Isoparaffin, Laureth-7, Phenoxyethanol, Caprylyl Glycol , Ethylhexylglycerin, Hexylene Glycol, Imperata Cylindrica Root Extract, PEG-8, Carbomer, Triethoxysilylethyl Polydimethylsiloxyethyl Hexyl Dimethicone, Cetyl Alcohol , Lecithin , Tocopherol , Ascorbyl Palmitate, Ascorbic Acid, Citric Acid , Xanthan Gum, Tocopheryl Linoleate/Oleate, Teprenone, Phoenix Dactylifera (Date) Fruit Extract , Polygonum Aviculare Extract, Sodium Lactate, Disodium EDTA, Dipotassium Glycyrrhizate, Arabidopsis Thaliana Extract, Plankton Extract , Micrococcus Lysate, Acrylates/C10-30 Alkyl Acrylate Crosspolymer , Tetrahexyldecyl Ascorbate , Bis(Cyano Butylacetate) Anthracenediylidene, Propylene Glycol , Caesalpinia spinosa Fruit Pod Extract , Helianthus Annuus(Sunflower) Sprout Extract, Sodium Benzoate , Potassium Sorbate, Rosa Damascena Flower Extract , 1,2-Hexanediol

PACKAGE LABEL

Manufacture for Dermaquest®, Inc.

Hayward, CA 94544

1272 GL, NL Made in USA

dermaquestinc.com